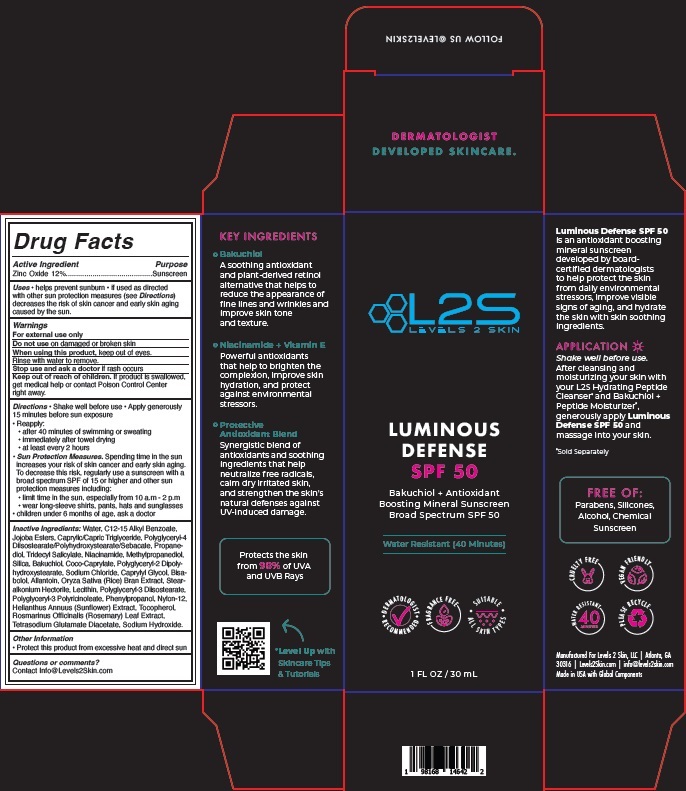 DRUG LABEL: Luminous Defense SPF 50
NDC: 84163-056 | Form: LOTION
Manufacturer: Levels 2 Skin
Category: otc | Type: HUMAN OTC DRUG LABEL
Date: 20240924

ACTIVE INGREDIENTS: ZINC OXIDE 120 mg/1 mL
INACTIVE INGREDIENTS: SILICON DIOXIDE; ALLANTOIN; LECITHIN, SUNFLOWER; SODIUM HYDROXIDE; POLYGLYCERYL-4 DIISOSTEARATE/POLYHYDROXYSTEARATE/SEBACATE; NIACINAMIDE; METHYLPROPANEDIOL; POLYGLYCERYL-3 PENTARICINOLEATE; TOCOPHEROL; WATER; HELIANTHUS ANNUUS FLOWERING TOP; POLYGLYCERYL-2 DIPOLYHYDROXYSTEARATE; CAPRYLYL GLYCOL; RICE BRAN; NYLON-12; TETRASODIUM GLUTAMATE DIACETATE; JOJOBA OIL, RANDOMIZED; PROPANEDIOL; PHENYLPROPANOL; ROSEMARY; ALKYL (C12-15) BENZOATE; MEDIUM-CHAIN TRIGLYCERIDES; TRIDECYL SALICYLATE; BAKUCHIOL; COCO-CAPRYLATE; SODIUM CHLORIDE; LEVOMENOL; STEARALKONIUM HECTORITE; POLYGLYCERYL-3 DIISOSTEARATE

Luminous Defense SPF 50

Active Ingredient

Zinc Oxide 12%

Purpose

Sunscreen

Uses

- helps prevent sunburn
- if used as directed with other sun protection measures (see Directions) decreases the risk of skin cancer and early skin aging caused by the sun.

Warnings

For external use only

Do not use

on damaged or broken skin

When using this product

keep out of eyes. Rinse with water to remove.

Stop use and ask a doctor

if rash occurs

Keep out of reach of children.

If product is swallowed, get medical help or contact Poison Control Center right away.

Directions

- Shake well before use
- Apply generously 15 minutes before sun exposure
- Reapply:
- after 40 minutes of swimming or sweating
- immediately after towel drying
- at least every 2 hours
- Sun Protection Measures. Spending time in the sun increases your risk of skin cancer and early skin aging. To decrease this risk, regularly use a sunscreen with a broad spectrum SPF of 15 or higher and other sun protection measures including:
- limit time in the sun, especially from 10 a.m. - 2 p.m.
- wear long-sleeve shirts, pants, hats and sunglasses
- children under 6 months of age, ask a doctor

Inactive Ingredients

Water, C12-15 Alkyl Benzoate, Jojoba Esters, Caprylic/Capric Triglyceride, Polyglyceryl-4 Diisostearate/Polyhydroxystearate/Sebacate, Propanediol, Tridecyl Salicylate, Niacinamide, Methylpropanediol, Silica, Bakuchiol, Coco-Caprylate, Polyglyceryl-2 Dipolyhydroxystearate, Sodium Chloride, Caprylyl Glycol, Bisabolol, Allantoin, Oryza Sativa (Rice) Bran Extract, Stearalkonium Hectorite, Lecithin, Polyglyceryl-3 Diisostearate, Polyglyceryl-3 Polyricinoleate, Phenylpropanol, Nylon-12, Helianthus Annuus (Sunflower) Extract, Tocopherol, Rosmarinus Officinalis (Rosemary) Leaf Extract, Tetrasodium Glutamate Diacetate, Sodium Hydroxide.

Other Information

- Protect this product from excessive heat and direct sun

Questions or comments?

Contact Info@Levels2Skin.com

Company Information

Manufactured For Levels 2 Skin, LLC | Atlanta, GA 30316 | Levels2Skin.com | info@levels2skin.com